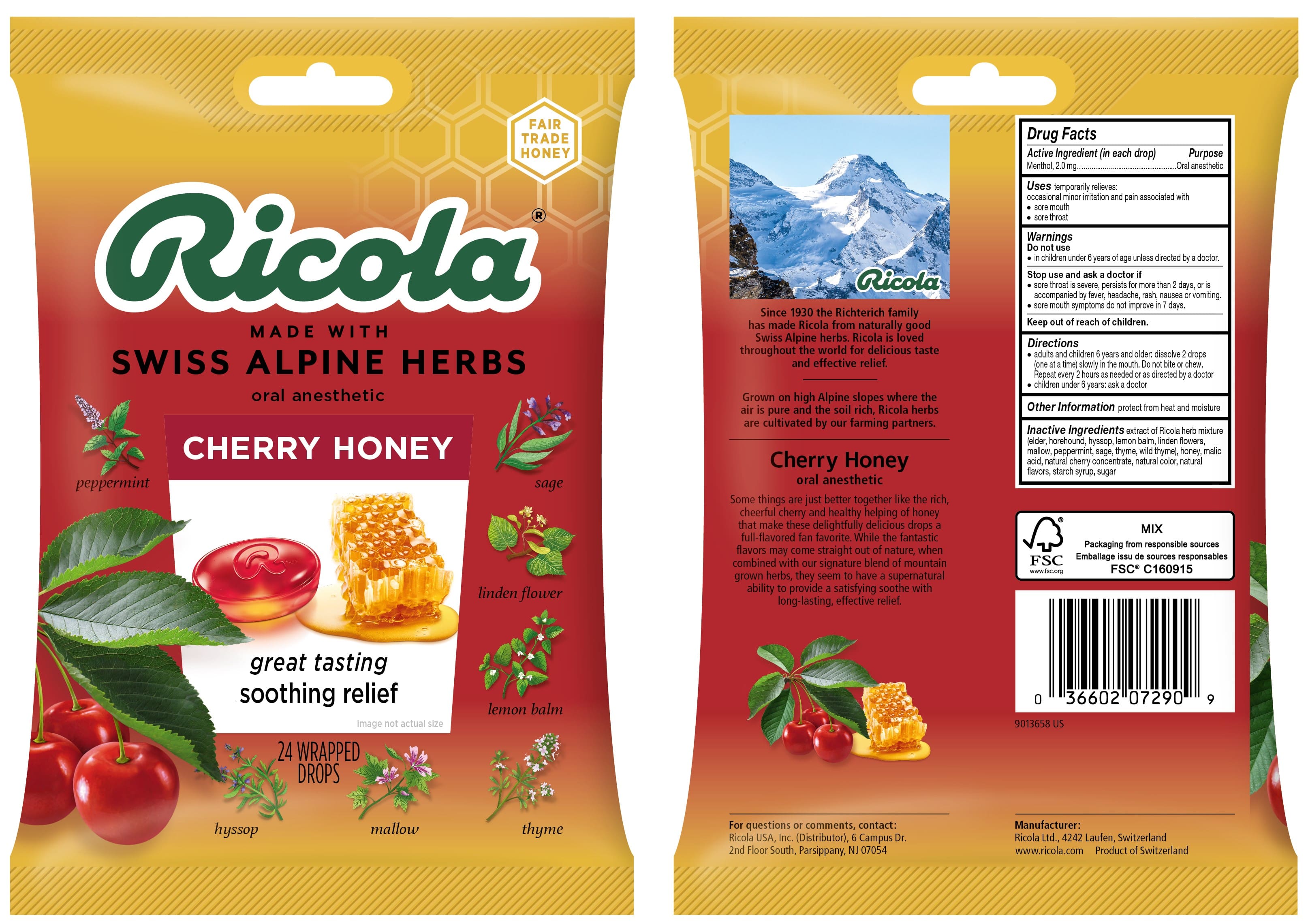 DRUG LABEL: Natural Cherry Honey Herb Throat Drops
NDC: 63667-953 | Form: LOZENGE
Manufacturer: Ricola USA Inc.
Category: otc | Type: HUMAN OTC DRUG LABEL
Date: 20241210

ACTIVE INGREDIENTS: MENTHOL 2.0 mg/1 1
INACTIVE INGREDIENTS: MALIC ACID; HONEY; CHERRY; SUCROSE

NATURAL CHERRY HONEY HERB THROAT DROPS

Drug Facts

Purpose

Oral anesthetic

Active Ingredient (in each drop)

Menthol, 2.0 mg

Uses

temporarily relieves occasional minor irritation and pain associated with:

- sore mouth
- sore throat

Warnings

Do not use

- in children under 6 years of age unless directed by a doctor.

Stop use and ask a doctor if

- sore throat is severe, persists for more than 2 days, or is accompanied by fever, headache, rash, nausea or vomiting
- sore mouth symptoms do not improve in 7 days

Directions

- adults and children 6 years and older: dissolve 2 drops (one at a time) slowly in the mouth. Repeat every 2 hours as needed or as directed by a doctor
- children under 6 years: ask a doctor

Other Information

Store in a dry place

Inactive Ingredients

extract of a Ricola herb mixture (elder, horehound, hyssop, lemon balm, linden flowers, mallow, peppermint, sage, thyme, wild thyme), honey, malic acid, natural cherry concentrate, natural color (extract of fruit and vegetable), natural flavors, starch syrup, sugar